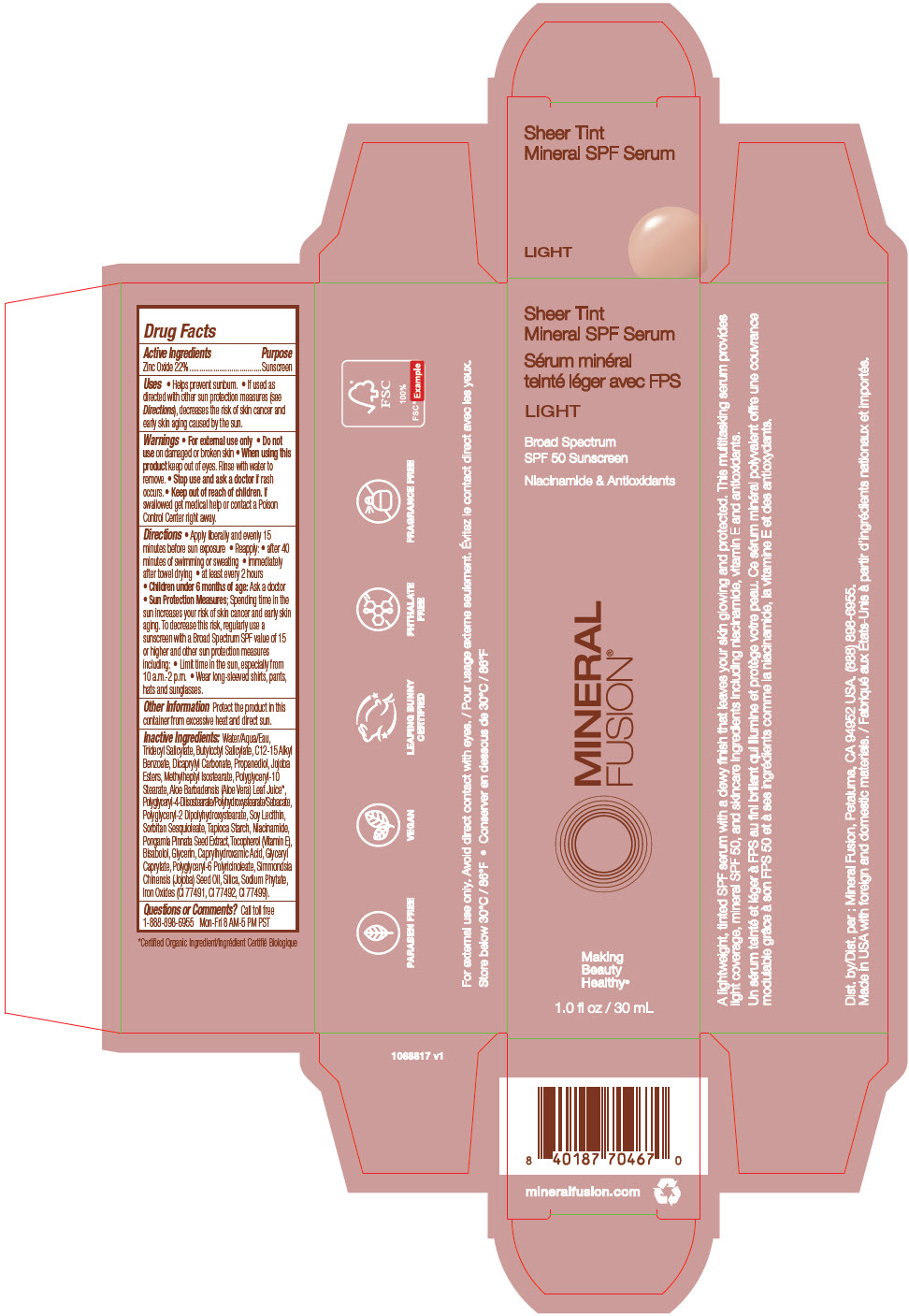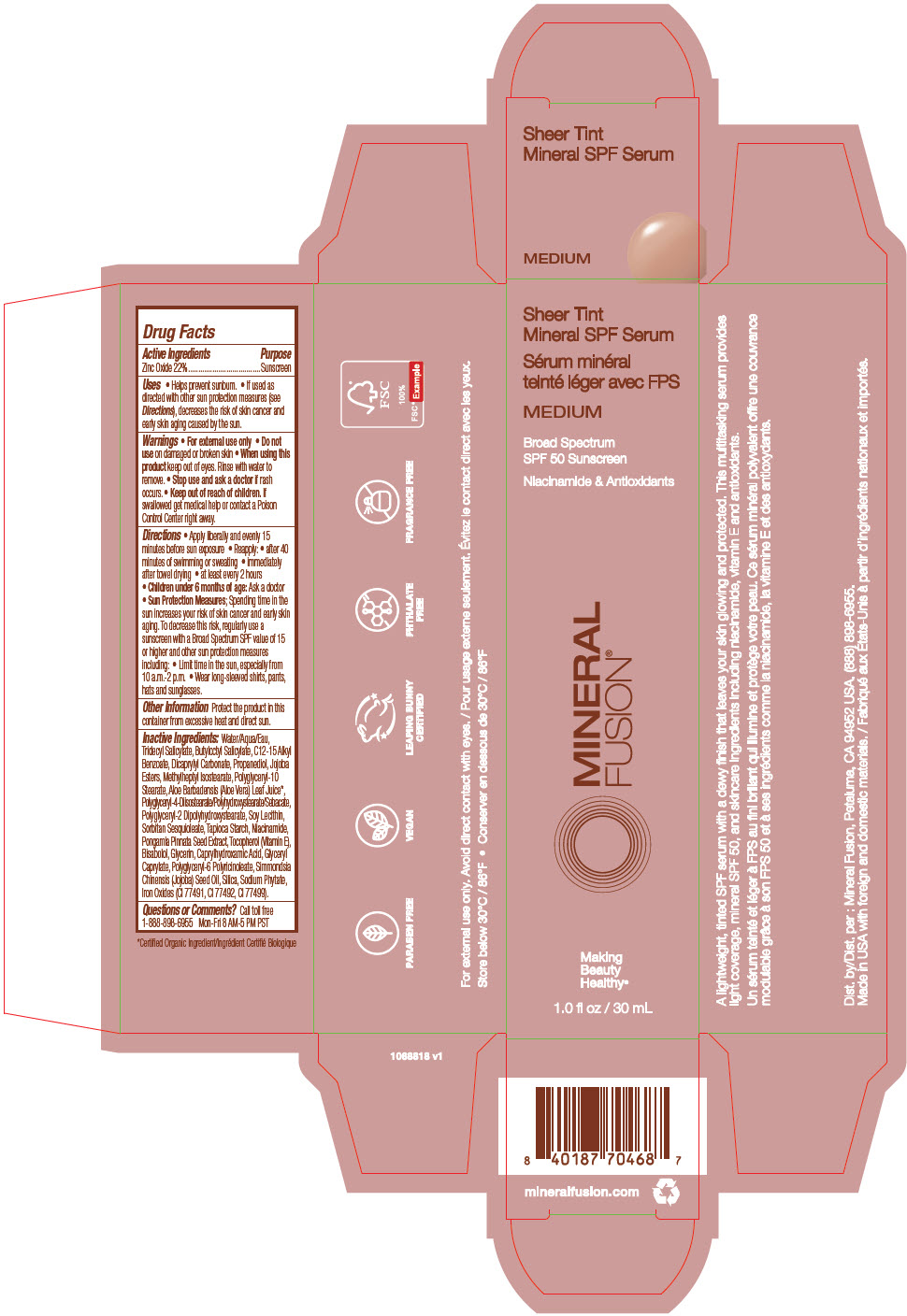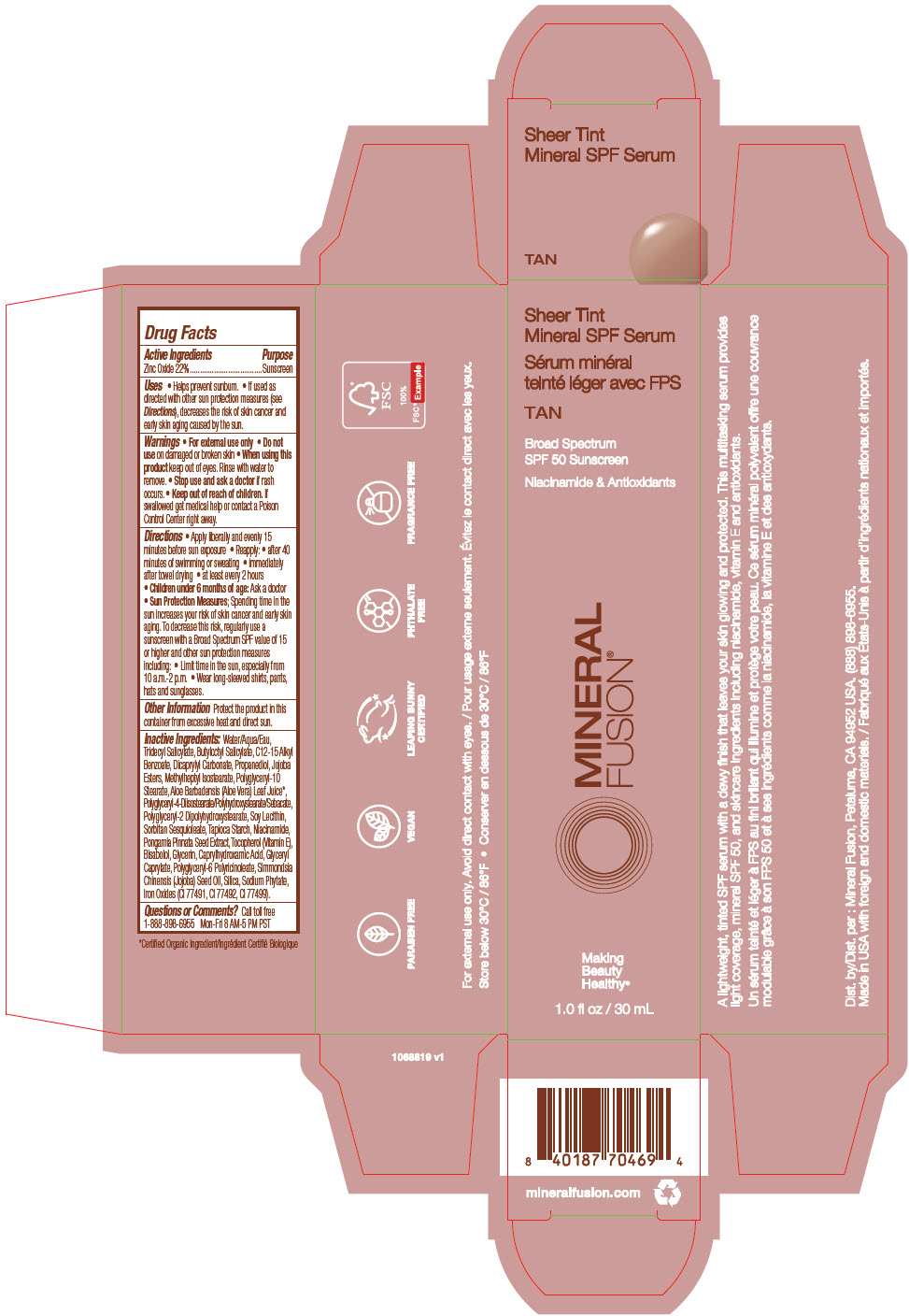 DRUG LABEL: Sheer Tint Mineral SPF Serum - Light
NDC: 55789-2501 | Form: LIQUID
Manufacturer: Mineral Fusion brands
Category: otc | Type: HUMAN OTC DRUG LABEL
Date: 20250214

ACTIVE INGREDIENTS: ZINC OXIDE 220 ug/1 g
INACTIVE INGREDIENTS: WATER; TRIDECYL SALICYLATE; BUTYLOCTYL SALICYLATE; ALKYL (C12-15) BENZOATE; DICAPRYLYL CARBONATE; PROPANEDIOL; HYDROLYZED JOJOBA ESTERS (ACID FORM); METHYLHEPTYL ISOSTEARATE; POLYGLYCERYL-10 STEARATE; POLYGLYCERYL-4 DIISOSTEARATE/POLYHYDROXYSTEARATE/SEBACATE; ALOE VERA LEAF; POLYGLYCERYL-2 DIPOLYHYDROXYSTEARATE; CAPRYLHYDROXAMIC ACID; GLYCERYL MONOCAPRYLATE; GLYCERIN; SOYBEAN LECITHIN; SORBITAN SESQUIOLEATE; STARCH, TAPIOCA; FERRIC OXIDE YELLOW; JOJOBA OIL; POLYGLYCERYL-6 POLYRICINOLEATE; SILICA DIMETHYL SILYLATE; PONGAMIA PINNATA SEED; TOCOPHEROL; .ALPHA.-BISABOLOL, (+)-; PHYTATE SODIUM; NIACINAMIDE

Sheer Tint Mineral SPF Serum

Drug Facts

Active Ingredients

Zinc Oxide 22%

Purpose

Sunscreen

Uses

- Helps prevent sunburn.
- If used as directed with other sun protection measures (see Directions), decreases the risk of skin cancer and early skin aging caused by the sun.

Warnings

- For external use only

- Do not use on damaged or broken skin

- When using this product keep out of eyes. Rinse with water to remove.

- Stop use and ask a doctor if rash occurs.

- Keep out of reach of children. If swallowed get medical help or contact a Poison Control Center right away.

Directions

- Apply liberally and evenly 15 minutes before sun exposure
- Reapply:
  - after 40 minutes of swimming or sweating
  - immediately after towel drying
  - at least every 2 hours
- Children under 6 months of age: Ask a doctor
- Sun Protection Measures; Spending time in the sun increases your risk of skin cancer and early skin aging. To decrease this risk, regularly use a sunscreen with a Broad Spectrum SPF value of 15 or higher and other sun protection measures including:
  - Limit time in the sun, especially from 10 a.m.-2 p.m.
  - Wear long-sleeved shirts, pants, hats and sunglasses.

Other Information

Protect the product in this container from excessive heat and direct sun.

Inactive Ingredients:

Water/Aqua/Eau, Tridecyl Salicylate, Butyloctyl Salicylate, C12-15 Alkyl Benzoate, Dicaprylyl Carbonate, Propanediol, Jojoba Esters, Methylheptyl Isostearate, Polyglyceryl-10 Stearate, Aloe Barbadensis (Aloe Vera) Leaf Juice [Certified Organic Ingredient] , Polyglyceryl-4-Diisostearate/Polyhydroxystearate/Sebacate, Polyglyceryl-2 Dipolyhydroxystearate, Soy Lecithin, Sorbitan Sesquioleate, Tapioca Starch, Niacinamide, Pongamia Pinnata Seed Extract, Tocopherol (Vitamin E), Bisabolol, Glycerin, Caprylhydroxamic Acid, Glyceryl Caprylate, Polyglyceryl-6 Polyricinoleate, Simmondsia Chinensis (Jojoba) Seed Oil, Silica, Sodium Phytate, Iron Oxides (CI 77491, CI 77492, CI 77499).

Questions or Comments?

Call toll free 1-888-898-6955 Mon-Fri 8 AM-5 PM PST

Dist. by : Mineral Fusion, Petaluma, CA 94952 USA.

PRINCIPAL DISPLAY PANEL - 30 mL Bottle Carton - LIGHT

Sheer Tint
Mineral SPF Serum

LIGHT

Broad Spectrum
SPF 50 Sunscreen

Niacinamide & Antioxidants

MINERAL
FUSION®

Making
Beauty
Healthy®

1.0 fl oz / 30 mL

PRINCIPAL DISPLAY PANEL - 30 mL Bottle Carton - MEDIUM

Sheer Tint
Mineral SPF Serum

MEDIUM

Broad Spectrum
SPF 50 Sunscreen

Niacinamide & Antioxidants

MINERAL
FUSION®

Making
Beauty
Healthy®

1.0 fl oz / 30 mL

PRINCIPAL DISPLAY PANEL - 30 mL Bottle Carton - TAN

Sheer Tint
Mineral SPF Serum

TAN

Broad Spectrum
SPF 50 Sunscreen

Niacinamide & Antioxidants

MINERAL
FUSION®

Making
Beauty
Healthy®

1.0 fl oz / 30 mL